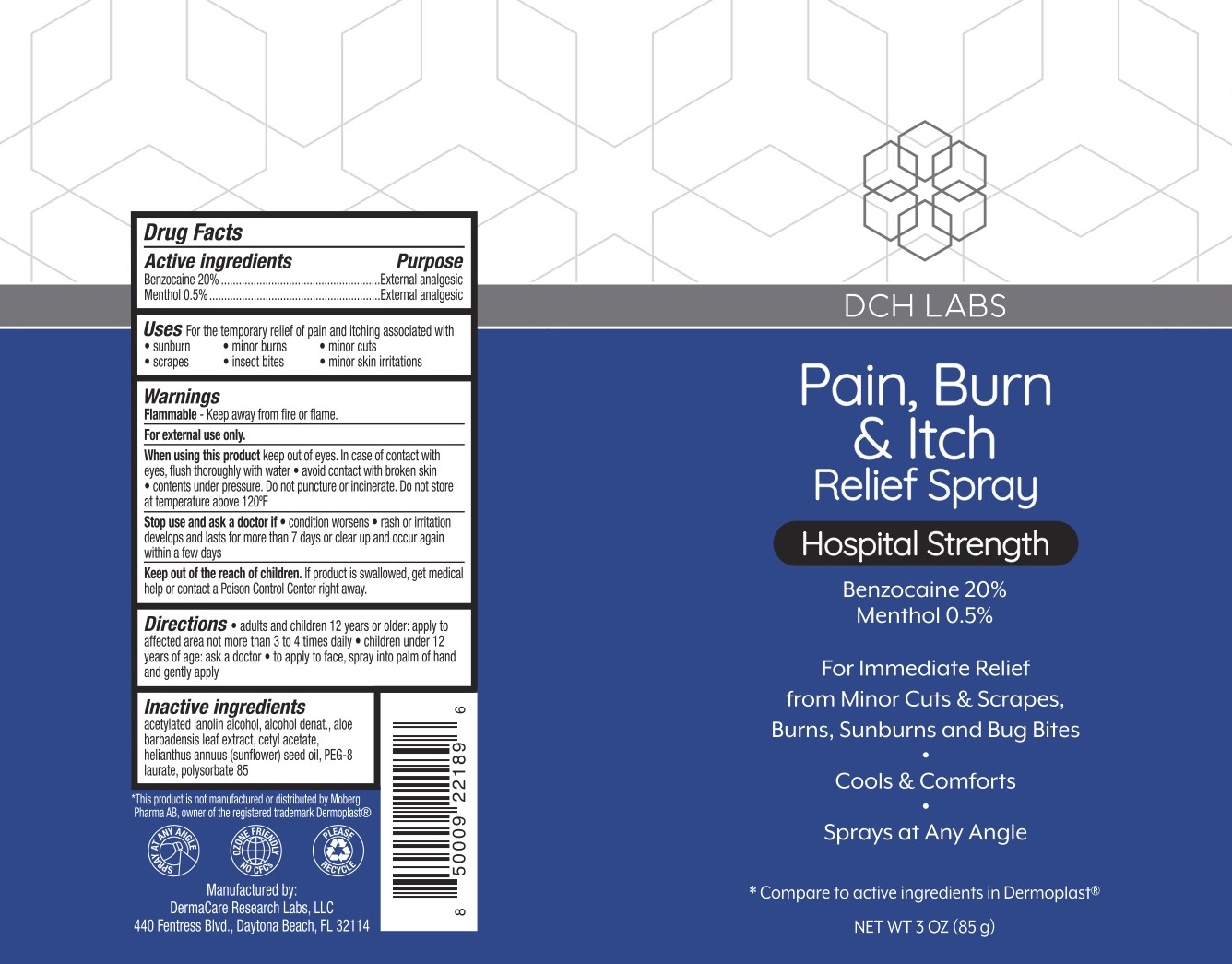 DRUG LABEL: Pain, Burn, and Itch Relief
NDC: 72839-343 | Form: SPRAY
Manufacturer: Derma Care Research Labs, LLC
Category: otc | Type: HUMAN OTC DRUG LABEL
Date: 20241219

ACTIVE INGREDIENTS: BENZOCAINE 20 g/100 g; MENTHOL 0.5 g/100 g
INACTIVE INGREDIENTS: ACETYLATED LANOLIN ALCOHOLS; ALCOHOL; CETYL ACETATE; SUNFLOWER OIL; PEG-8 LAURATE; POLYSORBATE 85; ALOE VERA LEAF

DCH Pain, Burn, Itch Spray

ACTIVE INGREDIENT

Benzocaine 20%, Menthol 0.5%

PURPOSE

Topical Analgesic

INDICATIONS AND USAGE

For the temporary relief of pain and itching associated with sunburn, minor skin irritations, insect bites, scrapes, minor cuts, and minor burns.

WARNINGS

For external use only. Flammable--Keep away from fire or flame. Allergyalert: do not use this product if you have a history of allergy to local anesthetics such as procaine, butacaine, benzocaine, or other "caine" anesthetics. When using this product avoid contact with eyes. Do not spray in the face or mouth. Use only as directed. Contents under pressure. Do not puncture or incinerate. Do not store at temperatures above 120F. Stop use and ask a doctor if condition worsens, if symptoms persist for more than 7 days or clear up and occur again within a few days, itching, rash or irritation develops.

KEEP OUT OF REACH OF CHILDREN

If swallowed, get medical help or contact a Poison Control Center right away.

DOSAGE AND ADMINISTRATION

Adults and children 2 years of age and older, apply to the affected area not more than 3 to 4 times daily. Children under 2 years of age: ask a doctor. To use this product, hold the can 6 to 12 inches away from the affected area. Direct spray nozzle towards skin and press the button to activate the spray. To apply to face, spray into palm of hand and gently apply.

INACTIVE INGREDIENT

Acetylated Lanolin Alcohol, Alcohol Denat., Aloe Barbadensis Leaf Extract, Cetyl Acetate, Helianthus Annuus (Sunflower) Seed Oil, PEG-8 Laurate, Polysorbate 85.